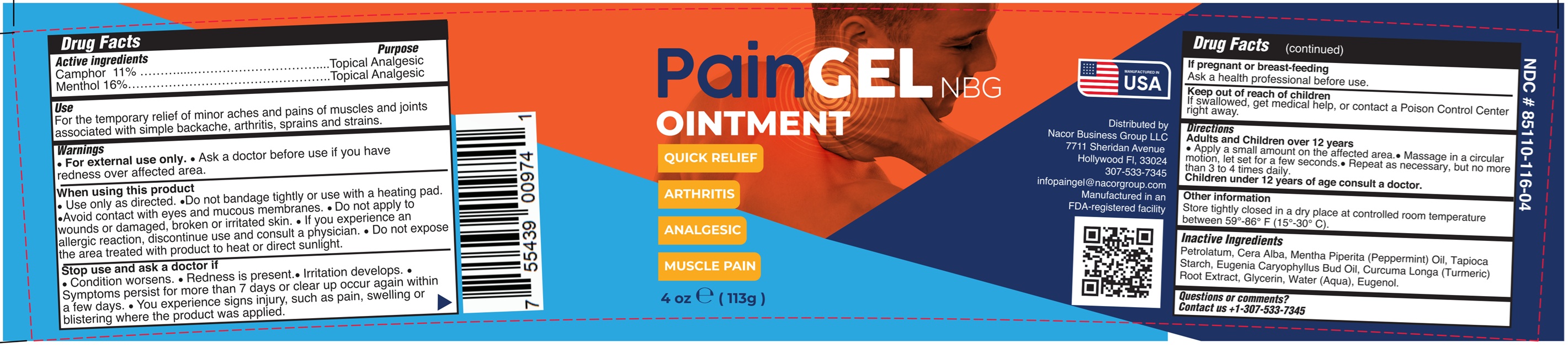 DRUG LABEL: PAINGEL UNGUENTO
NDC: 85110-116 | Form: OINTMENT
Manufacturer: NACOR BUSINESS GROUP LLC
Category: otc | Type: HUMAN OTC DRUG LABEL
Date: 20251106

ACTIVE INGREDIENTS: CAMPHOR (SYNTHETIC) 11 g/100 g; MENTHOL 16 g/100 g
INACTIVE INGREDIENTS: GLYCERIN; WATER; PETROLATUM; WHITE WAX; MENTHA PIPERITA (PEPPERMINT) OIL; TAPIOCA STARCH; EUGENIA CARYOPHYLLUS (CLOVE) BUD OIL; CURCUMA LONGA (TURMERIC) ROOT; EUGENOL

85110-116-04

Active ingredients

Camphor 11%

Menthol 16%

Purpose

Topical Analgesic

Use

for temporary local relief of minor pains of muscles and joints associated with simple backache, arthritis, sprains and strains.

Warnings

- For external use only.
- Ask a doctor before use if you have redness over affected area.

When using this product

- Use only as directed.
- Do not bandage tightly or use with a heating pad.
- Avoid contact with eyes and mucous membranes.
- Do not apply to wounds or damaged, broken or irritated skin.
- If you experience an allergic reaction, discontinue use and consult a physician.
- Do not expose the area treated with product to heat or direct sunlight.

Stop use and ask a doctor if

- Condition worsens.
- Redness is present.
- Irritation develops.
- Symptoms persist for more than 7 days or clear up occur again within a few days.
- You experience signs injury, such as pain, swelling or blistering where the product was applied.

If pregnant or breast – feeding

Ask a health professional before use.

Keep out of reach of children.

If swallowed, get medical help, or contact a Poison Control Center right away.

Directions

Adults and Children over 12 years of age:

- Apply a small amount on the affected area.
- Massage in a circular motion, let set for a few seconds.
- Repeat as necessary, but no more than 3 to 4 times daily.

Children under 12 years of age; do not use, consult a doctor.

Other information

Store tightly closed in a dry place at controlled room temperature between 59°F - 86°F (15°C - 30°C)

Inactive ingredients

Petrolatum, Cera Alba, Mentha Piperita (Peppermint) Oil, Tapioca Starch, Eugenia Caryophyllus Bud Oil, Curcuma Longa (Turmeric) Root Extract, Glycerin, Water (Aqua), Eugenol.

Questions or comments?

Contact us +1-307-533-7345